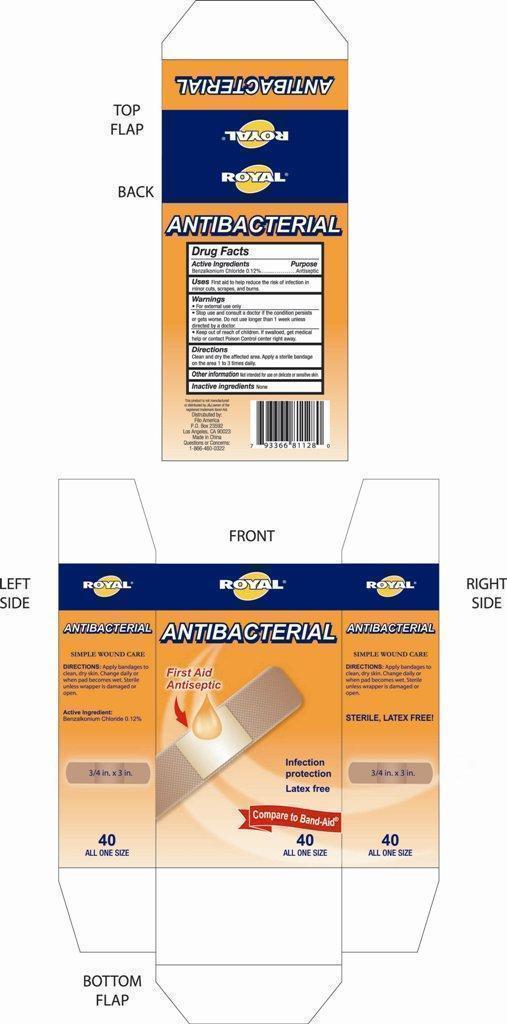 DRUG LABEL: ANTIBACTERIAL BANDAGE
NDC: 50438-128 | Form: SWAB
Manufacturer: Filo America
Category: otc | Type: HUMAN OTC DRUG LABEL
Date: 20130816

ACTIVE INGREDIENTS: BENZALKONIUM CHLORIDE 0.12 g/100 g
INACTIVE INGREDIENTS: WATER

Active Ingredients

Benzalkonium Chloride 0.12%

Purpose

Antiseptic

Use

First aid to help reduce the risk of infection in minor cuts ,scrapes,and burns.

Warnings

For external use only.

Stop use and consult a doctor if the dondition persists or gets worse .Do not use longer than 1 week unless directed by a doctor.

Keep out of reach of children.if swallowed get medical help or contact Poison control Center right away.

Directions

Clean and dry the affected area .Apply a sterile bandage on the area 1 to 3 times daily.

Other information :not intended for use on delicate or sensitive skin.

Inactive Ingredient

None